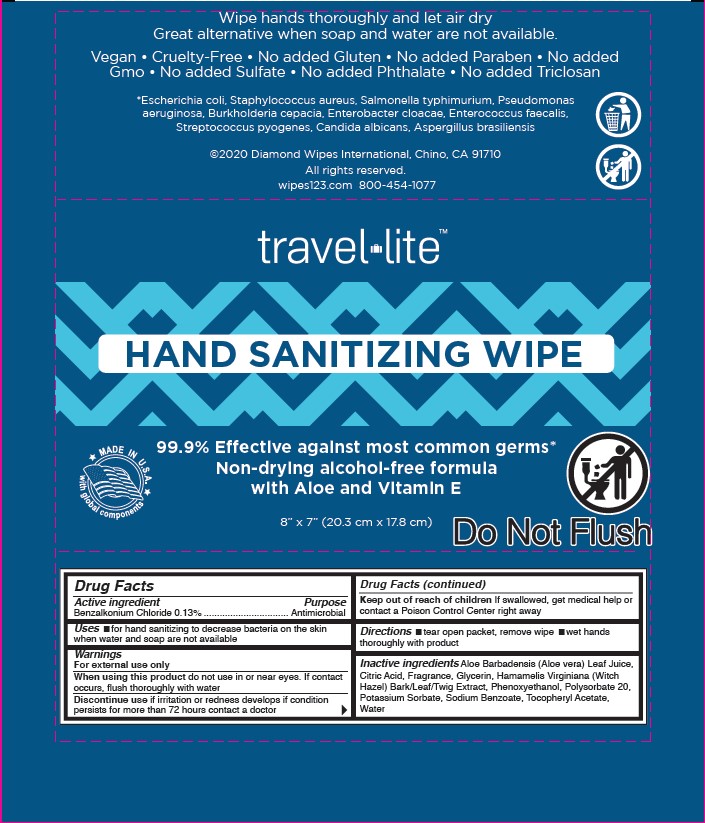 DRUG LABEL: Travel lite Hand Sanitizing Wipes
NDC: 64709-107 | Form: CLOTH
Manufacturer: Diamond Wipes International, Inc
Category: otc | Type: HUMAN OTC DRUG LABEL
Date: 20251125

ACTIVE INGREDIENTS: BENZALKONIUM CHLORIDE 0.13 g/100 g
INACTIVE INGREDIENTS: ALOE VERA LEAF; WATER; CITRIC ACID MONOHYDRATE; GLYCERIN; HAMAMELIS VIRGINIANA TOP; PHENOXYETHANOL; POLYSORBATE 20; POTASSIUM SORBATE; SODIUM BENZOATE; .ALPHA.-TOCOPHEROL ACETATE

Travel Lite Hand Sanitizing Wipes

Active ingredient

Benzalkonium Chloride 0.13%

Purpose

Antimicrobial

Uses

■ for hand sanitizing to decrease bacteria on the skin when water and soap are not available

Warnings

For external use only

When using this product do not use in or near eyes. If contact occurs, flush thoroughly with water

Discontinue use if irritation or redness develops if condition persists for more than 72 hours contact a doctor

Keep out of reach of children If swallowed, get medical help or contact a Poison Control Center right away

Directions

■ tear open packet, remove wipe ■ wet hands thoroughly with product

Inactive ingredients

Aloe Barbadensis (Aloe vera) Leaf Juice, Citric Acid, Fragrance, Glycerin, Hamamelis Virginiana (Witch Hazel) Bark/Leaf/Twig Extract, Phenoxyethanol, Polysorbate 20, Potassium Sorbate, Sodium Benzoate, Tocopheryl Acetate, Water

Label

Wipe hands thoroughly and let air dry
Great alternative when soap and water are not available.

Vegan • Cruelty-Free • No added Gluten • No added Paraben • No added
Gmo • No added Sulfate • No added Phthalate • No added Triclosan

*Escherichia coli, Staphylococcus aureus, Salmonella typhimurium, Pseudomonas
aeruginosa, Burkholderia cepacia, Enterobacter cloacae, Enterococcus faecalis,
Streptococcus pyogenes, Candida albicans, Aspergillus brasiliensis

©2020 Diamond Wipes International, Chino, CA 91710
All rights reserved.
wipes123.com 800-454-1077

travel lite™

HAND SANITIZING WIPE

MAKE IN U.S.A. with global components

99.9% Effective against most common germs*
Non-drying alcohol-free formula
with Aloe and Vitamin E

8” x 7” (20.3 cm x 17.8 cm)

Do Not Flush

Drug Facts
Active ingredient Purpose
Benzalkonium Chloride 0.13% ................. Antimicrobial

Uses ■ for hand sanitizing to decrease bacteria on the skin when water and soap are not available

Warnings
For external use only
When using this product do not use in or near eyes. If contact occurs, flush thoroughly with water
Discontinue use if irritation or redness develops if condition persists for more than 72 hours contact a doctor

Drug Facts (continued)

Keep out of reach of children If swallowed, get medical help or contact a Poison Control Center right away

Directions ■ tear open packet, remove wipe ■ wet hands thoroughly with product

Inactive ingredients Aloe Barbadensis (Aloe vera) Leaf Juice, Citric Acid, Fragrance, Glycerin, Hamamelis Virginiana (Witch Hazel) Bark/Leaf/Twig Extract, Phenoxyethanol, Polysorbate 20, Potassium Sorbate, Sodium Benzoate, Tocopheryl Acetate, Water